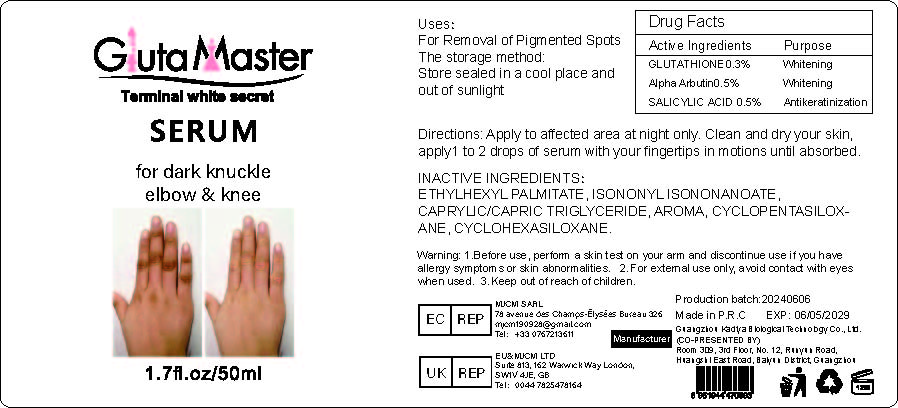 DRUG LABEL: Dark knucklee SERUM
NDC: 84423-004 | Form: OIL
Manufacturer: Guangzhou Kadiya Biotechnology Co., Ltd.
Category: otc | Type: HUMAN OTC DRUG LABEL
Date: 20240627

ACTIVE INGREDIENTS: ALPHA-ARBUTIN 0.25 mg/50 mg; GLUTATHIONE 0.25 mg/50 mg; SALICYLIC ACID 0.15 mg/50 mg
INACTIVE INGREDIENTS: ISONONYL ISONONANOATE; CYCLOMETHICONE 5; CYCLOMETHICONE 6; ETHYLHEXYL PALMITATE

ACTIVIE INGREDIENT

GLUTATHIONE 0.3%
Alpha Arbutin 0.5%
SALICYLIC ACID 0.5%

INACTIVE INGREDIENT

ETHYLHEXYL PALMITATE, ISONONYL ISONONANOATE, CAPRYLIC/CAPRIC TRIGLYCERIDE, AROMA, CYCLOPENTASILOXANE, CYCLOHEXASILOXANE

PURPOSE

For Removal of Pigmented Spots

WARNING

1.Before use, perform a skin test on your arm and discontinue use if you have allergy symptoms or skin abnormalities.
2、For external use only, avoid contact with eyes when used
3、Keep out of reach of children

INSTRUCTIONS FOR USE

Apply to affected area at night only. Clean and dry your skin, apply1 to 2 drops of serum with your fingertips in motions until absorbed

DOSAGE

Apply to affected area at night only. Clean and dry your skin,
apply1 to 2 drops of serum with your fingertips in motions until absorbed.

Warning

Keep out of reach of children

USAGE

For Removal of Pigmented Spots

PACKAGE LABEL

Terminal white secret SERUM for dark knuckleelbow & knee

1. Active Ingredients
GLUTATHIONE0.3%
Alpha Arbutin0.5%
SALICYLIC ACID 0.5%

2.Purpose
For Removal of Pigmented Spots

3.Inactive ingredients:
ETHYLHEXYL PALMITATE, ISONONYL ISONONANOATE, CAPRYLIC/CAPRIC TRIGLYCERIDE, AROMA, CYCLOPENTASILOXANE, CYCLOHEXASILOXANE

4.Warning
1.Before use, perform a skin test on your arm and discontinue use if you have allergy symptoms or skin abnormalities.
2. For external use only, avoid contact with eyes when used.
3. Keep out of reach of children.

5.Instructions for use
Apply to affected area at night only. Clean and dry your skin, apply1 to 2 drops of serum with your fingertips in motions until absorbed